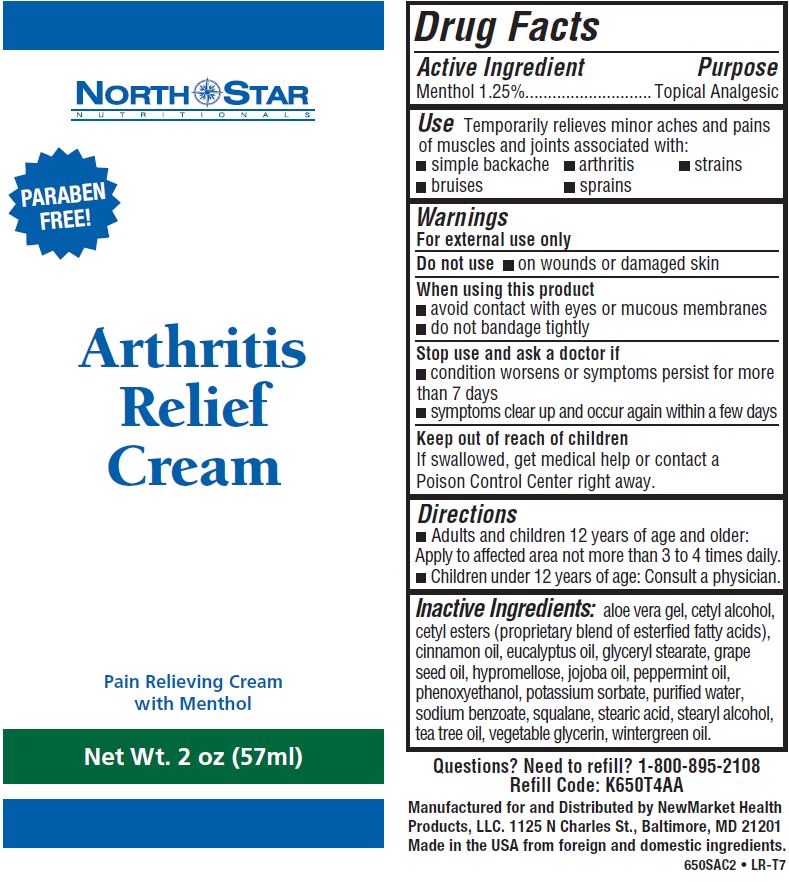 DRUG LABEL: Arthritis Relief
NDC: 50972-274 | Form: CREAM
Manufacturer: NewMarket Health Products LLC
Category: otc | Type: HUMAN OTC DRUG LABEL
Date: 20171004

ACTIVE INGREDIENTS: MENTHOL 12.5 mg/1 mL
INACTIVE INGREDIENTS: ALOE VERA LEAF; CETYL ALCOHOL; CETYL ESTERS WAX; CINNAMON OIL; EUCALYPTUS OIL; GLYCERYL MONOSTEARATE; GRAPE SEED OIL; HYPROMELLOSES; JOJOBA OIL; PEPPERMINT OIL; POTASSIUM SORBATE; WATER; SQUALANE; STEARIC ACID; STEARYL ALCOHOL; TEA TREE OIL; GLYCERIN; METHYL SALICYLATE; PHENOXYETHANOL; SODIUM BENZOATE

Arthritis Relief Cream

Active Ingredient

Menthol 1.25%

Purpose

Topical Analgesic

INDICATIONS AND USAGE

Use Temporarily relieves minor aches and pains of muscles and joints associated with:

- simple backache
- arthritis
- strains
- bruises
- sprains

Directions

- Adult and children 12 years of age and older: Apply to affected area not more than 3 to 4 times daily.
- Children under 12 years of age: Consult a physician.

INACTIVE INGREDIENT

Inactive Ingredients: aloe vera gel, cetyl alcohol, cetyl esters (proprietary blend of esterfied fatty acids), cinnamon oil, eucalyptus oil, glyceryl stearate, grape seed oil, hypromellose, jojoba oil, peppermint oil, phenoxyethanol, potassium sorbate, purified water, sodium benzoate, squalane, stearic acid, stearyl alcohol, tea tree oil, vegetable glycerin, wintergreen oil.

Questions? Need to Refill? 1-800-895-2108

Refill Code: K650T4AA

Manufactured for and Distributed by NewMarket Health

Products, LLC. 1125 N. Charles St., Baltimore, MD 21201

Made in the USA from foreign and domestic ingredients.

Warnings

For external use only

Do not use

- on wounds or damaged skin

When using this product

- avoid contact with eyes or mucous membranes
- do not bandage tightly

Stop use and ask a doctor if

- condition worsens or symptoms persist for more than 7 days
- symptoms clear up and occur again within a few days

Keep out of reach of children
If swallowed, get medical help or contact a Poison Control Center right away.

PACKAGE LABEL

North Star

Nutritionals

PARABEN FREE!

Arthritis Relief Cream

Pain Relieving Cream

with Menthol

Net Wt. 2 oz (57ml)